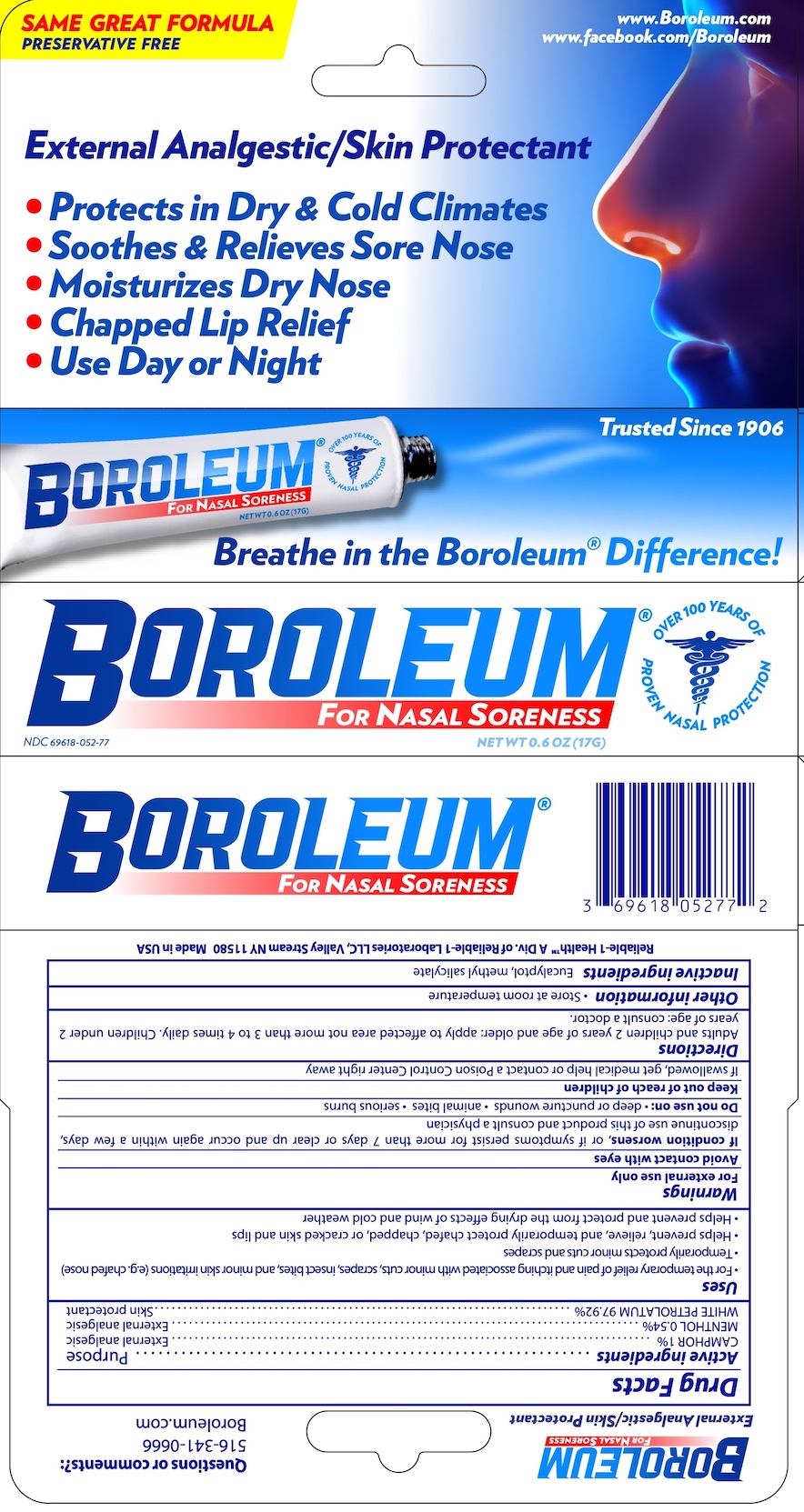 DRUG LABEL: Boroleum
NDC: 69618-052 | Form: OINTMENT
Manufacturer: Reliable 1 Laboratories
Category: otc | Type: HUMAN OTC DRUG LABEL
Date: 20250115

ACTIVE INGREDIENTS: WHITE PETROLATUM 97.92 g/100 g; CAMPHOR (SYNTHETIC) 1 g/100 g; MENTHOL 0.54 g/100 g
INACTIVE INGREDIENTS: EUCALYPTOL; METHYL SALICYLATE

Boroleum

Questions or comments?:

516-341-0666

Boroleum.com

Drug Facts

Active ingredients

CAMPHOR 1%

MENTHOL 0.54%

WHITE PETROLATUM 97.92%

Purpose

External analgesic

External analgesic

Skin protectant

Uses

- For the temporary relief of pain and itching associated with minor cuts, scrapes, insect bites, and minor skin irritations (e.g. chafed nose)
- Temporarily protects minor cuts and scrapes
- Helps prevent, relieve, and temporarily protect chafed, chapped, or cracked skin and lips
- Helps prevent and protect from the drying effects of wind and cold weather

Warnings

For external use only

WHEN USING

Avoid contact with eyes.

STOP USE

If condition worsens, or if symptoms persist for more than 7 days or clear up and occur again within a few days, discontinue use of this product and consult a physician

Do not use on:

- deep or puncture wounds
- animal bites
- serious burns

Keep out of reach of children. If swallowed, get medical help or contact a Poison Control Center right away.

Directions

Adults and children 2 years of age and older: apply to affected area not more than 3 to 4 times daily. Children under 2 years of age: consult a doctor.

Other information

- Store at room temperature

Inactive ingredients

Eucalyptol, methyl salicylate

Reliable-1 Laboratories LLC Valley Stream NY 11580 Made for Reliable-1 in US

PACKAGE LABEL

External Analgestic/Skin Protectant

Protects in Dry & Cold Climates
Soothes and Relieves Sore Nose
Moisturizes Dry Nose
Chapped Lip Relief
Use Day or Night

BOROLEUM®

FOR NASAL SORENESS

NDC 69618-052-77

NET WT 0.6 OZ (17G)